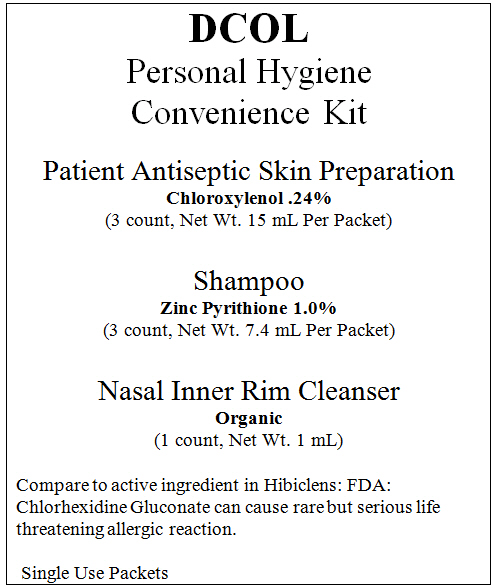 DRUG LABEL: D-COL Personal Hygiene Convenience kit
NDC: 53205-001 | Form: KIT | Route: TOPICAL
Manufacturer: D-COL Inc
Category: otc | Type: HUMAN OTC DRUG LABEL
Date: 20250114

ACTIVE INGREDIENTS: Pyrithione Zinc 10 mg/1 mL; Chloroxylenol 2.4 mg/1 mL
INACTIVE INGREDIENTS: Water; CARBOMER INTERPOLYMER TYPE A (ALLYL SUCROSE CROSSLINKED); SODIUM LAURETH-3 SULFATE; PEG-90 Diisostearate; Cocamidopropyl Betaine; COCO DIETHANOLAMIDE; CYCLOMETHICONE 5; EDETATE SODIUM; CAPRYLYL GLYCOL; Sodium Hydroxide; Propylene Glycol; COCO DIETHANOLAMIDE; Ammonium Lauryl Sulfate; SODIUM LAURETH-3 SULFATE; CITRIC ACID MONOHYDRATE; EDETIC ACID; Ammonium Chloride; Propylparaben; IMIDUREA; Water

D-COL Personal Hygiene Convenience Kit

D-COL Patient Antiseptic Skin Preparation

Drug Facts

Active Ingredient

Chloroxylenol 0.24%

Purpose

Antiseptic

Uses

- Antiseptic skin cleansers help reduce bacteria that potentially causes disease.
- For patient antiseptic skin preparation (15 mL packets only).
- For healthcare personnel hand wash.
- For surgical hand scrub.

WARNINGS

Do not use

- If you or the patient is allergic to Chloroxylenol or any other ingredient in this product.

When using this product

- Keep out of eyes, ears, and mouth. May cause serious and permanent eye injury if permitted to enter and remain in the eye or may cause deafness when instilled in the middle ear through perforated eardrums.
- If contact occurs in any of these areas, rinse with cold water right away.
- Repeated general cleansing of large body areas should not be done except when advised by a health care provider.

Stop use and ask doctor if irritation, sensitization, or allergic reaction occurs.

Keep out of reach of children. If swallowed, get medical help or contact a Poison Control Center right away.

Directions

- Patient antiseptic skin preparation. Thoroughly rinse the area to be cleansed with water. Apply the minimum amount of the product necessary to cover the skin area and wash gently. Rinse thoroughly with water.
- Surgical hand scrub. Wet hands and forearms with water. Scrub for 3 minutes with about 5 mL of the product with a brush. Rinse thoroughly under running water.
- Healthcare personnel handwash. Wet hands with water. Dispense about 5 mL of the product into cupped hands and wash in a vigorous manner for 15 seconds. Rinse and dry thoroughly.

Other Information

- Store between 20-25°C (68-77°F).
- Avoid excessive heat above 40°C (104°F).

Inactive Ingredient

propylene glycol, cocamide dea, ammonium lauryl sulfate, sodium laureth sulfate, citric acid, edta, ammonium chloride, propylparaben, imidazolidinyl urea, fragrance, deionized water

Net Wt. 15 mL per packet

Distributed by: D-COL, Inc. 219 East Craig Place San Antonio, TX 78212

Questions?

(210)-227-3612

D-COL Nasal Inner Rim Cleanser

Uses

For nasal inner rim cleanser.

Warnings

For use only in the inner rim of each nostril.

When using this product

Avoid contact with eyes. In case of eye contact, flush with water.

Stop use and ask doctor if irritation, discomfort, or redness develops.

Keep out of reach of children. If swallowed, get medical help or contact a Poison Control Center right away.

Directions

- Apply a reasonable amount of the product to the end of your index finger for a single nasal inner rim application.
- Save a reasonable amount to apply to the opposite nasal inner rim.
- Insert your index finger into one nostril no further than the inner rim, and cover the inner rim of the nasal passage with the product.
- Do not apply the product beyond the inner rim of the nasal passage.
- Repeat the application of the product to the untreated nasal inner rim.
- Wait 30 seconds after you complete the application, and thoroughly wipe the inner rim of each nostril with a cloth wet with water.
- Children under 6 years of age should be supervised when using this product.

Inactive Ingredient

benzalkonium chloride, polysorbate 20, peach kernel oil glycereth-8 esters, sodium chloride, potassium sorbate, sodium citrate, xylitol, disodium edta, lavandula angustifolia (lavender) oil, mentha viridis (spearmint leaf) oil, melaleuca alternifolia (tea tree leaf) oil, citric acid

Net Wt. 1 mL per packet

Distributed by: D-COL, Inc. 219 East Craig Place San Antonio, TX 78212

Questions?

(210)-227-3612

D-COL Shampoo

Drug Facts

Active Ingredient

Zinc Pyrithione 1.0%

Purpose

Anti-dandruff

Uses

helps prevent recurrence of flaking and itching associated with dandruff.

Warnings

For external use only.

When using this product

Avoid contact with eyes. If contact occurs, rinse eyes thoroughly with water.

Stop use and ask doctor if condition worsens or does not improve after regular use of this product as directed.

Keep out of reach of children. If swallowed, get medical help or contact a Poison Control Center right away.

Directions

- Place enough product in your palm to thoroughly cover the scalp area.
- Rub hands together until product covers entire surface of your palms.
- Apply product to the scalp and thoroughly massage and cover the scalp.
- Rinse with water until the product is completely removed from the application area.
- Use one packet as directed.
- Children under 6 years of age should be supervised when using this product.

Inactive Ingredient

deionized water, acrylates/C10-30 alkyl acrylate crosspolymer, sodium lauryl ether sulfate, PEG-90 diisostearate, cocamidopropyl betaine, cocamide dea, cyclomethicone 5, edta sodium, caprylyl glycol, sodium hydroxide

Net Wt. 7.4 mL per packet

Distributed by: D-COL, Inc. 219 East Craig Place San Antonio, TX 78212

Questions?

(210)-227-3612

PRINCIPAL DISPLAY PANEL - Kit Carton Label

DCOL
Personal Hygiene
Convenience Kit

Patient Antiseptic Skin Preparation
Chloroxylenol .24%
(3 count, Net Wt. 15 mL Per Packet)

Shampoo
Zinc Pyrithione 1.0%
(3 count, Net Wt. 7.4 mL Per Packet)

Nasal Inner Rim Cleanser
Organic
(1 count, Net Wt. 1 mL)

Compare to active ingredient in Hibiclens: FDA:
Chlorhexidine Gluconate can cause rare but serious life
threatening allergic reaction.

Single Use Packets